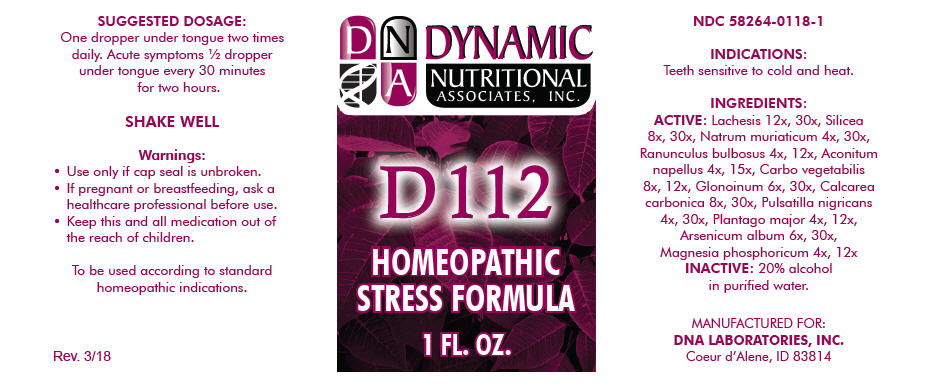 DRUG LABEL: D-112
NDC: 58264-0118 | Form: SOLUTION
Manufacturer: DNA Labs, Inc.
Category: homeopathic | Type: HUMAN OTC DRUG LABEL
Date: 20250113

ACTIVE INGREDIENTS: LACHESIS MUTA VENOM 12 [hp_X]/1 mL; SILICON DIOXIDE 8 [hp_X]/1 mL; SODIUM CHLORIDE 4 [hp_X]/1 mL; RANUNCULUS BULBOSUS 4 [hp_X]/1 mL; ACONITUM NAPELLUS 4 [hp_X]/1 mL; ACTIVATED CHARCOAL 8 [hp_X]/1 mL; NITROGLYCERIN 6 [hp_X]/1 mL; OYSTER SHELL CALCIUM CARBONATE, CRUDE 8 [hp_X]/1 mL; ANEMONE PRATENSIS 4 [hp_X]/1 mL; PLANTAGO MAJOR 4 [hp_X]/1 mL; ARSENIC TRIOXIDE 6 [hp_X]/1 mL; MAGNESIUM PHOSPHATE, DIBASIC TRIHYDRATE 4 [hp_X]/1 mL
INACTIVE INGREDIENTS: ALCOHOL; WATER

D-112

NDC 58264-0118-1

INDICATIONS

PURPOSE

Teeth sensitive to cold and heat.

INGREDIENTS

ACTIVE

Lachesis 12x, 30x, Silicea 8x, 30x, Natrum muriaticum 4x, 30x, Ranunculus bulbosus 4x, 12x, Aconitum napellus 4x, 15x, Carbo vegetabilis 8x, 12x, Glonoinum 6x, 30x, Calcarea carbonica 8x, 30x, Pulsatilla nigricans 4x, 30x, Plantago major 4x, 12x, Arsenicum album 6x, 30x, Magnesia phosphoricum 4x, 12x

INACTIVE

20% alcohol in purified water.

SUGGESTED DOSAGE

One dropper under tongue two times daily. Acute symptoms ½ dropper under tongue every 30 minutes for two hours.

STORAGE AND HANDLING

SHAKE WELL

Warnings

- Use only if cap seal is unbroken.

PREGNANCY OR BREAST FEEDING

- If pregnant or breastfeeding, ask a healthcare professional before use.

KEEP OUT OF REACH OF CHILDREN

- Keep this and all medication out of the reach of children.

To be used according to standard homeopathic indications.

PRINCIPAL DISPLAY PANEL - 1 FL. OZ. Bottle Label

DYNAMIC
NUTRITIONAL
ASSOCIATES, INC.

D 112

HOMEOPATHIC
STRESS FORMULA

1 FL. OZ.